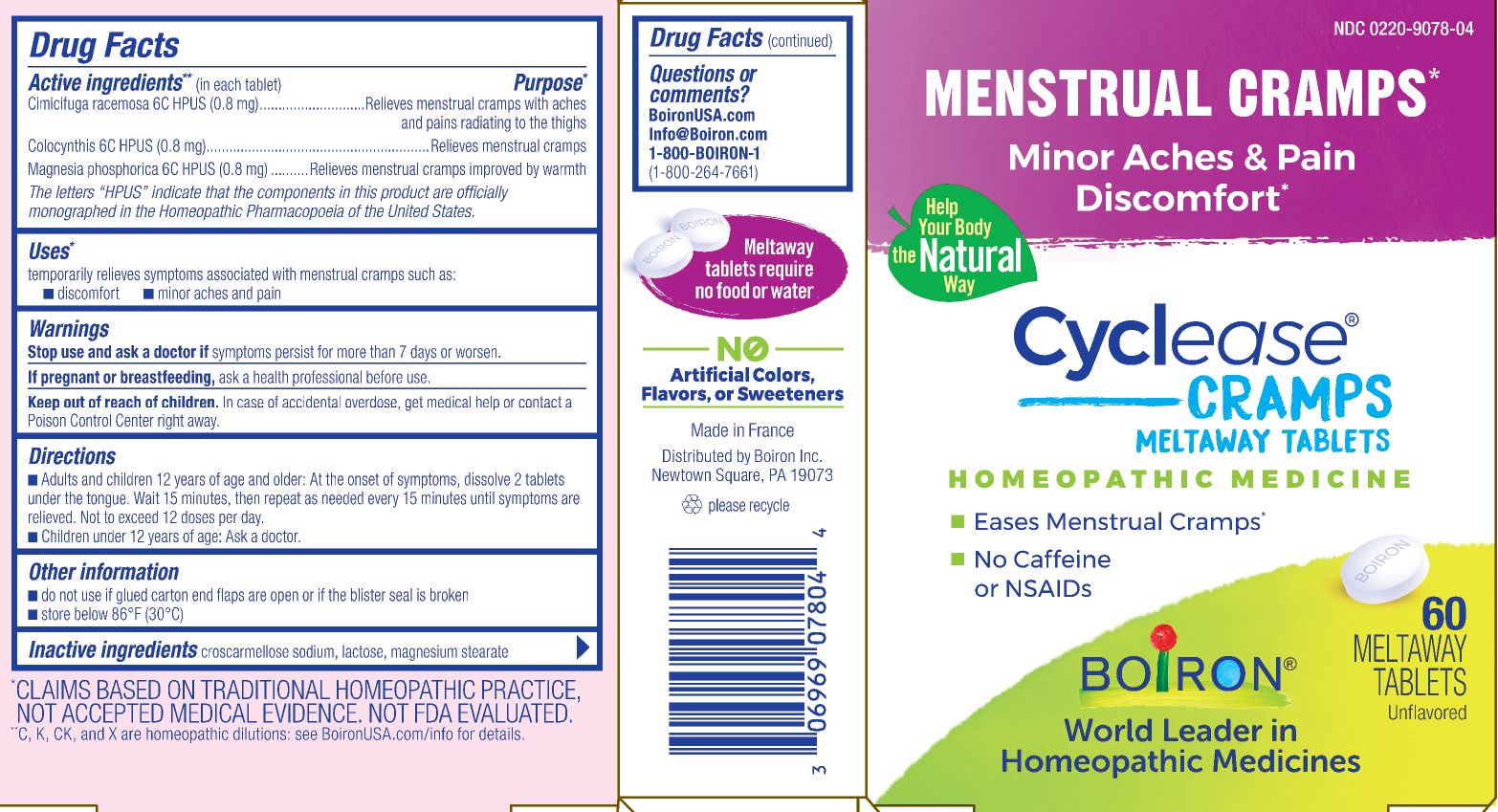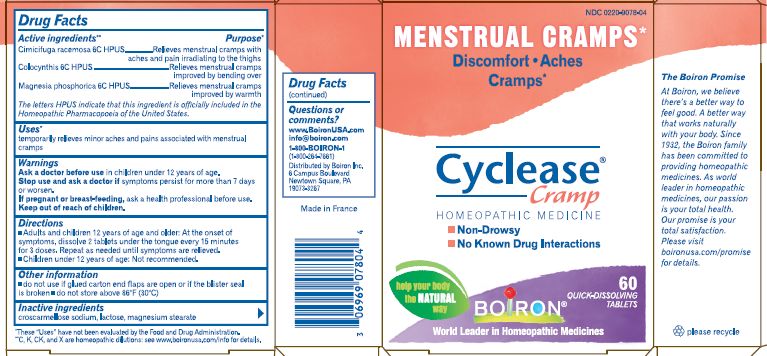 DRUG LABEL: Cyclease Cramps
NDC: 0220-9078 | Form: TABLET
Manufacturer: Laboratoires Boiron
Category: homeopathic | Type: HUMAN OTC DRUG LABEL
Date: 20230306

ACTIVE INGREDIENTS: BLACK COHOSH 6 [hp_C]/1 1; CITRULLUS COLOCYNTHIS FRUIT PULP 6 [hp_C]/1 1; MAGNESIUM PHOSPHATE, DIBASIC TRIHYDRATE 6 [hp_C]/1 1
INACTIVE INGREDIENTS: CROSCARMELLOSE SODIUM; LACTOSE; MAGNESIUM STEARATE

Cyclease Cramp

ACTIVE INGREDIENT

Cimicifuga racemosa 6C HPUS (0.8mg), Colcynthis 6C HPUS (0.8mg), Magnesia phosphorica 6C HPUS *0.8mg)

INDICATIONS AND USAGE

Temporarily relieves symptoms associated with menstrual cramps such as: discomfort, minor aches and pain

Do not use if glued carton en flaps are open or if the blister seal is broken

DOSAGE AND ADMINISTRATION

Adults and children 12 years of age and older: At the onset of symptoms, dissolve 2 tablets under the tongue. Wait 15 minutes, the repeat as needed every 15 minutes until symptoms are relieved. Not to exceed 12 doses per day.

Children until 12 of age: Ask a doctor.

INACTIVE INGREDIENT

Croscarmellose sodium, lactose, magnesium stearate

HOW SUPPLIED

60 tablets

PURPOSE

Cimicifuga racemosa 6C ...Relieves menstrual cramps with aches and pains radiating to the thighs
Colcynthis 6C...Relieves menstrual cramps

Magnesia phosphorica 6C... Relieves menstrual cramps improved by warmth

STORAGE AND HANDLING

Store at 68-77o F

Questions, Comments
Boironusa.com
info@boironusa.com
1-800-BOIRON-1
(1-800-264-7661)
Distributed by Boiron, Inc.

Newtown Square, PA 19073

Stop use and ask a doctor if symptoms persist for more than 7 days or worsen.

Keep out of reach of children
In case of accidental overdose, get medical help or contact a Poison Control Center right away.

PREGNANCY OR BREAST FEEDING

If pregnant or breast-feeding, ask a health professional before use.

DRUG INTERACTIONS

Safe - no side effects - no drug interactions - works naturally with your body

WARNINGS

Enter section text here

*CLAIMS BASED ON TRADITIONAL HOMEOPATHIC PRACTICE NOT ACCEPTED MEDICAL EVIDENCE. NOT FDA EVALUATED.
**C,K,CK, and X are homeopathic dilutions: see BoironUSA.com/info for details.

The letters "HPUS" indicate that the components in this product are officially monographed in the Homeopathic Pharmacopoeia of the United States.